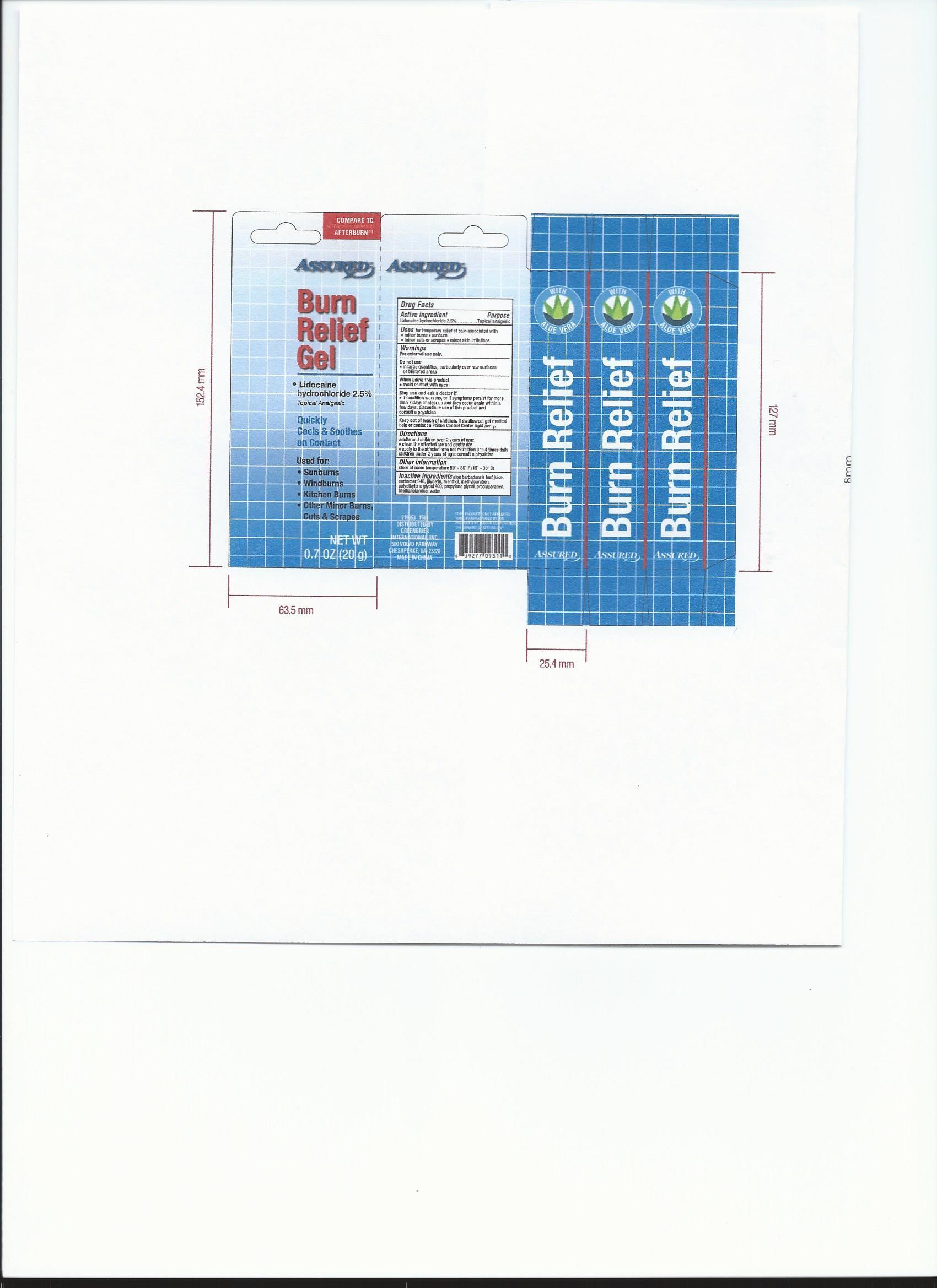 DRUG LABEL: Assured
NDC: 55621-010 | Form: GEL
Manufacturer: Zhejiang Jingwei Pharmaceutical Co., Ltd.
Category: otc | Type: HUMAN OTC DRUG LABEL
Date: 20231025

ACTIVE INGREDIENTS: LIDOCAINE HYDROCHLORIDE 2.5 g/100 g
INACTIVE INGREDIENTS: CARBOMER HOMOPOLYMER TYPE C (ALLYL PENTAERYTHRITOL CROSSLINKED); PROPYLENE GLYCOL; TROLAMINE; POLYETHYLENE GLYCOL, UNSPECIFIED; GLYCERIN; MENTHOL, UNSPECIFIED FORM; METHYLPARABEN; PROPYLPARABEN; ALOE VERA LEAF; WATER

Drug Facts

Inactive Ingredients aloe barbadensis leaf juice, carbomer 940,

glycerin, menthol, methylparaben, polyethylene glycol 400,

propylene glycol, propylparaben, triethanolamine, water

Active Ingredient

Lidocaine hydrochloride 2.5 %

Purpose

Topical analgesic

INDICATIONS AND USAGE

Uses for temporary relief of pain associated with

- minor burns

- sunburn

- minor cuts or scrapes

- minor skin irritations

Warnings

For external use only

Do not use

- in large quantities, particularly over raw surfaces

or blistered areas

When using this product

- avoid contact with eyes

Stop use and ask a doctor if

- if condition worsens, or if symptoms persist for more than 7 days

or clear up and then occur again within a few days, discontinue use

of this product and consult a physician

Keep out of reach of children. If swallowed, get medical help

or contact a Poison Control Center right away

Directions

adults and children under 2 years of age:

- clean the affected area and gently dry

- apply to the affected area not more than 3 to 4 times daily

children udner 2 years of age: consult a physician

Other Information

store at room temperature 59 - 86 F (15 C - 30 C)